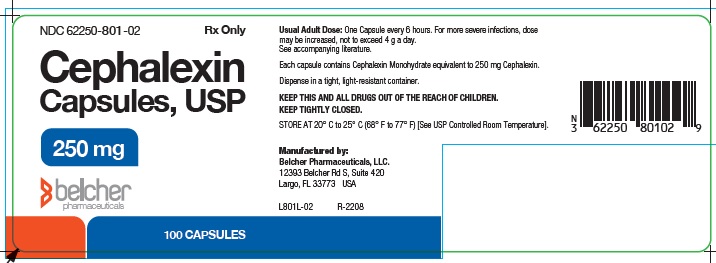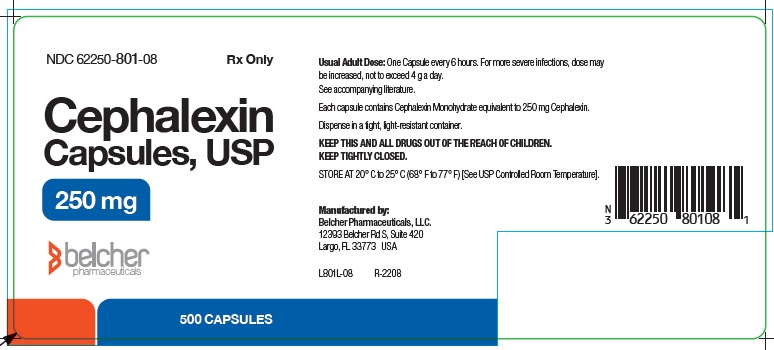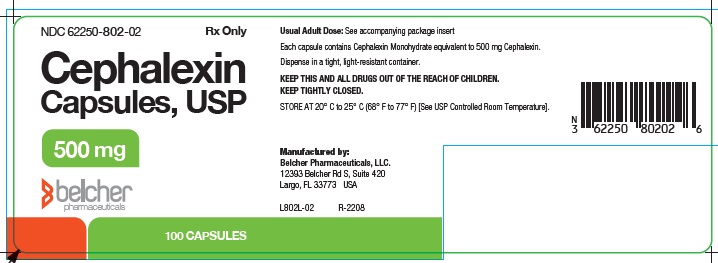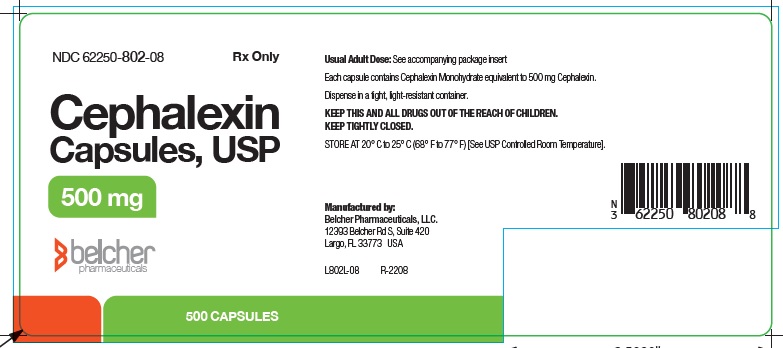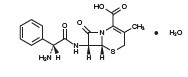 DRUG LABEL: Cephalexin
NDC: 62250-801 | Form: CAPSULE
Manufacturer: Belcher Pharmaceuticals, LLC
Category: prescription | Type: HUMAN PRESCRIPTION DRUG LABEL
Date: 20250211

ACTIVE INGREDIENTS: CEPHALEXIN 250 mg/1 1
INACTIVE INGREDIENTS: ANHYDROUS LACTOSE; GELATIN; MAGNESIUM STEARATE; TALC; TITANIUM DIOXIDE

CEPHALEXIN CAPSULES, USP

To reduce the development of drug-resistant bacteria and maintain the effectiveness of cephalexin and other antibacterial drugs, cephalexin should be used only to treat or prevent infections that are proven or strongly suspected to be caused by bacteria.

DESCRIPTION

Cephalexin, USP is a semisynthetic cephalosporin antibiotic intended for oral administration. It is 7-(D-α-Amino-α-phenylacetamido)-3-methyl-3-cephem-4-carboxylic acid monohydrate. Cephalexin has the molecular formula C16H17N3O4S H2O and the molecular weight is 365.41.

Cephalexin has the following structural formula:

The nucleus of cephalexin is related to that of other cephalosporin antibiotics. The compound is a zwitterion; i.e., the molecule contains both a basic and an acidic group. The isoelectric point of cephalexin in water is approximately 4.5 to 5.

The crystalline form of cephalexin which is available is a monohydrate. It is a white crystalline solid having a bitter taste. Solubility in water is low at room temperature; 1 or 2 mg/mL may be dissolved readily, but higher concentrations are obtained with increasing difficulty.

The cephalosporins differ from penicillins in the structure of the bicyclic ring system. Cephalexin has a D-phenylglycyl group as substituent at the 7-amino position and an unsubstituted methyl group at the 3-position.

Each capsule contains cephalexin monohydrate equivalent to 250 mg or 500 mg of cephalexin. The capsules also contain anhydrous lactose, gelatin, magnesium stearate, talc and titanium dioxide. The capsules are imprinted with edible ink containing black iron oxide.

CLINICAL PHARMACOLOGY

Human Pharmacology

Cephalexin is acid stable and may be given without regard to meals. It is rapidly absorbed after oral administration. Following doses of 250 mg, 500 mg, and 1 g, average peak serum levels of approximately 9, 18, and 32 µg/mL respectively were obtained at 1 hour. Measurable levels were present 6 hours after administration. Cephalexin is excreted in the urine by glomerular filtration and tubular secretion. Studies showed that over 90% of the drug was excreted unchanged in the urine within 8 hours. During this period, peak urine concentrations following the 250 mg, 500 mg, and 1g doses were approximately 1000, 2200, and 5000 µg/mL respectively.

Microbiology

In vitrotests demonstrate that the cephalosporins are bactericidal because of their inhibition of cell-wall synthesis. Cephalexin has been shown to be active against most strains of the following microorganisms both in vitroand in clinical infections as described in the INDICATIONS AND USAGEsection.

Aerobes, Gram-positive:

- Staphylococcus aureus(including penicillinase-producing strains)
  Streptococcus pneumoniae(penicillin-susceptible strains)
  Streptococcus pyogenes

Aerobes, Gram-negative:

- Escherichia coli
  Haemophilus influenzae
  Klebsiella pneumoniae
  Moraxella (Branhamella) catarrhalis
  Proteus mirabilis

Note:Methicillin-resistant staphylococci and most strains of enterococci (Enterococcusfaecalis[formerly Streptococcus faecalis]) are resistant to cephalosporins, including cephalexin. It is not active against most strains of Enterobacterspp., Morganellamorganii, and Proteus vulgaris. It has no activity against Pseudomonasspp. or Acinetobacter calcoaceticus. Penicillin-resistant Streptococcus pneumoniaeis usually cross-resistant to beta-lactam antibiotics.

Susceptibility Tests

Dilution techniques— Quantitative methods are used to determine antimicrobial minimal inhibitory concentrations (MIC’s). These MIC’s provide estimates of the susceptibility of bacteria to antimicrobial compounds. The MIC’s should be determined using a standardized procedure. Standardized procedures are based on a dilution method^1-3(broth or agar) or equivalent with standardized inoculum concentrations and standardized concentrations of cephalothin powder. The MIC values should be interpreted according to the following criteria:

MIC (µg/mL) | Interpretation
≤8 | Susceptible | (S)
16 | Intermediate | (I)
≥32 | Resistant | (R)

A report of "Susceptible" indicates that the pathogen is likely to be inhibited if the antimicrobial compound in the blood reaches the concentrations usually achievable. A report of "Intermediate" indicates that the result should be considered equivocal, and, if the microorganism is not fully susceptible to alternative, clinically feasible drugs, the test should be repeated. This category implies possible clinical applicability in body sites where the drug is physiologically concentrated or in situations where high dosage of drug can be used. This category also provides a buffer zone which prevents small uncontrolled technical factors from causing major discrepancies in interpretation. A report of "Resistant" indicates that the pathogen is not likely to be inhibited if the antimicrobial compound in the blood reaches the concentrations usually achievable; other therapy should be selected.

Standardized susceptibility test procedures require the use of laboratory control microorganisms to control the technical aspects of the laboratory procedures. Standard cephalothin powder should provide the following MIC values:

Microorganism |  | MIC (µg/mL)
E. coli | ATCC 25922 | 4 to 16
S. aureus | ATCC 29213 | 0.12 to 0.5

Diffusion techniques— Quantitative methods that require measurement of zone diameters also provide reproducible estimates of the susceptibility of bacteria to antimicrobial compounds. One such standardized procedure^2,3requires the use of standardized inoculum concentrations. This procedure uses paper disks impregnated with 30µg cephalothin to test the susceptibility of microorganisms to cephalexin.

Reports from the laboratory providing results of the standard single-disk susceptibility test with a 30 µg cephalothin disk should be interpreted according to the following criteria:

Zone Diameter (mm) | Interpretation
≥18 | Susceptible | (S)
15 to 17 | Intermediate | (I)
≤14 | Resistant | (R)

Interpretation should be as stated above for results using dilution techniques. Interpretation involves correlation of the diameter obtained in the disk test with the MIC for cephalexin.

As with standard dilution techniques, diffusion methods require the use of laboratory control microorganisms that are used to control the technical aspects of the laboratory procedures. For the diffusion technique, the 30µg cephalothin disk should provide the following zone diameters in these laboratory test quality control strains:

Microorganism |  | Zone Diameter (mm)
E. coli | ATCC 25922 | 15 to 21
S. aureus | ATCC 29213 | 29 to 37

INDICATIONS AND USAGE

Cephalexin capsules are indicated for the treatment of the following infections when caused by susceptible strains of the designated microorganisms:

Respiratory tract infections caused by Streptococcus pneumoniaeand Streptococcus

pyogenes(Penicillin is the usual drug of choice in the treatment and prevention of streptococcal infections, including the prophylaxis of rheumatic fever. Cephalexin is generally effective in the eradication of streptococci from the nasopharynx; however, substantial data establishing the efficacy of cephalexin in the subsequent prevention of rheumatic fever are not available at present.)

Otitis media due to Streptococcus pneumoniae, Haemophilus influenzae, Staphylococcus aureus, Streptococcus pyogenes, and Moraxella catarrhalis

Skin and skin structure infections caused by Staphylococcus aureusand/or Streptococcus pyogenes

Bone infections caused by Staphylococcus aureusand/or Proteus mirabilis

Genitourinary tract infections, including acute prostatitis, caused by Escherichia coli, Proteus mirabilis,and Klebsiella pneumoniae

Note:Culture and susceptibility tests should be initiated prior to and during therapy. Renal function studies should be performed when indicated.

To reduce the development of drug-resistant bacteria and maintain the effectiveness of cephalexin and other antibacterial drugs, cephalexin capsules should be used only to treat or prevent infections that are proven or strongly suspected to be caused by susceptible bacteria. When culture and susceptibility information are available, they should be considered in selecting or modifying antibacterial therapy. In the absence of such data, local epidemiology and susceptibility patterns may contribute to the empiric selection of therapy.

CONTRAINDICATIONS

Cephalexin capsules are contraindicated in patients with known allergy to the cephalosporin group of antibiotics.

WARNINGS

BEFORE THERAPY WITH CEPHALEXIN IS INSTITUTED, CAREFUL INQUIRY SHOULD BE MADE TO DETERMINE WHETHER THE PATIENT HAS HAD PREVIOUS HYPERSENSITIVITY REACTIONS TO CEPHALEXIN, CEPHALOSPORINS, PENICILLINS, OR OTHER DRUGS. IF THIS PRODUCT IS TO BE GIVEN TO PENICILLIN-SENSITIVE PATIENTS, CAUTION SHOULD BE EXERCISED BECAUSE CROSS-HYPERSENSITIVITY AMONG BETA-LACTAM ANTIBIOTICS HAS BEEN CLEARLY DOCUMENTED AND MAY OCCUR IN UP TO 10% OF PATIENTS WITH A HISTORY OF PENICILLIN ALLERGY. IF AN ALLERGIC REACTION TO CEPHALEXIN OCCURS, DISCONTINUE THE DRUG. SERIOUS ACUTE HYPERSENSITIVITY REACTIONS MAY REQUIRE TREATMENT WITH EPINEPHRINE AND OTHER EMERGENCY MEASURES, INCLUDING OXYGEN, INTRAVENOUS FLUIDS, INTRAVENOUS ANTIHISTAMINES, CORTICOSTEROIDS, PRESSOR AMINES AND AIRWAY MANAGEMENT, AS CLINICALLY INDICATED.

There is some clinical and laboratory evidence of partial cross-allergenicity of the penicillins and the cephalosporins. Patients have been reported to have had severe reactions (including anaphylaxis) to both drugs.

Any patient who has demonstrated some form of allergy, particularly to drugs, should receive antibiotics cautiously. No exception should be made with regard to cephalexin capsules.

Clostridium difficileassociated diarrhea (CDAD)has been reported with use of nearly all antibacterial agents, including cephalexin, and may range in severity from mild diarrhea to fatal colitis. Treatment with antibacterial agents alters the normal flora of the colon leading to overgrowth of C. difficile.

C. difficileproduces toxins A and B which contribute to the development of CDAD. Hypertoxin producing strains of C. difficilecause increased morbidity and mortality, as these infections can be refractory to antimicrobial therapy and may require colectomy. CDAD must be considered in all patients who present with diarrhea following antibiotic use. Careful medical history is necessary since CDAD has been reported to occur over two months after the administration of antibacterial agents.

If CDAD is suspected or confirmed, ongoing antibiotic use not directed against C. difficilemay need to be discontinued. Appropriate fluid and electrolyte management, protein supplementation, antibiotic treatment of C. difficile, and surgical evaluation should be instituted as clinically indicated.

PRECAUTIONS

General

Prescribing cephalexin capsules in the absence of a proven or strongly suspected bacterial infection or a prophylactic indication is unlikely to provide benefit to the patient and increases the risk of the development of drug-resistant bacteria.

Patients should be followed carefully so that any side effects or unusual manifestations of drug idiosyncrasy may be detected. If an allergic reaction to cephalexin occurs, the drug should be discontinued and the patient treated with the usual agents (e.g., epinephrine or other pressor amines, antihistamines, or corticosteroids).

Prolonged use of cephalexin capsules may result in the overgrowth of nonsusceptible organisms. Careful observation of the patient is essential. If superinfection occurs during therapy, appropriate measures should be taken.

Positive direct Coombs’ tests have been reported during treatment with the cephalosporin antibiotics. In hematologic studies or in transfusion cross-matching procedures when antiglobulin tests are performed on the minor side or in Coombs’ testing of newborns whose mothers have received cephalosporin antibiotics before parturition, it should be recognized that a positive Coombs’ test may be due to the drug.

Cephalexin capsules should be administered with caution in the presence of markedly impaired renal function. Under such conditions, careful clinical observation and laboratory studies should be made because safe dosage may be lower than that usually recommended.

Indicated surgical procedures should be performed in conjunction with antibiotic therapy.

Broad-spectrum antibiotics should be prescribed with caution in individuals with a history of gastrointestinal disease, particularly colitis.

Cephalosporins may be associated with a fall in prothrombin activity. Those at risk include patients with renal or hepatic impairment, or poor nutritional state, as well as patients receiving a protracted course of antimicrobial therapy, and patients previously stabilized on anticoagulant therapy. Prothrombin time should be monitored in patients at risk and exogenous vitamin K administered as indicated.

Information for Patients

Patients should be counseled that antibacterial drugs including cephalexin should only be used to treat bacterial infections. They do not treat viral infections (e.g., the common cold). When cephalexin is prescribed to treat a bacterial infection, patients should be told that although it is common to feel better early in the course of therapy, the medication should be taken exactly as directed. Skipping doses or not completing the full course of therapy may (1) decrease the effectiveness of the immediate treatment and (2) increase the likelihood that bacteria will develop resistance and will not be treatable by cephalexin or other antibacterial drugs in the future.

Diarrhea is a common problem caused by antibiotics which usually ends when the antibiotic is discontinued. Sometimes after starting treatment with antibiotics, patients can develop watery and bloody stools (with or without stomach cramps and fever) even as late as two or more months after having taken the last dose of the antibiotic. If this occurs, patients should contact their physician as soon as possible.

Drug Interactions

Metformin— In healthy subjects given single 500 mg doses of cephalexin and metformin, plasma metformin mean Cmaxand AUC increased by an average of 34% and 24%, respectively, and metformin mean renal clearance decreased by 14%. No information is available about the interaction of cephalexin and metformin following multiple doses of either drug.

Although not observed in this study, adverse effects could potentially arise from co¬administration of cephalexin and metformin by inhibition of tubular secretion via organic cationic transporter systems. Accordingly, careful patient monitoring and dose adjustment of metformin is recommended in patients concomitantly taking cephalexin and metformin.

Probenecid— As with other β-lactams, the renal excretion of cephalexin is inhibited by probenecid.

Drug / Laboratory Test Interactions

As a result of administration of cephalexin capsules, a false-positive reaction for glucose in the urine may occur. This has been observed with Benedict’s and Fehling’s solutions and also with Clinitest®tablets.

Carcinogenesis, Mutagenesis, Impairment of Fertility

Lifetime studies in animals have not been performed to evaluate the carcinogenic potential of cephalexin. Tests to determine the mutagenic potential of cephalexin have not been performed. In male and female rats, fertility and reproductive performance were not affected by cephalexin oral doses up to 1.5 times the highest recommended human dose based upon mg/m^2.

Pregnancy

Teratogenic effects — Pregnancy Category B— Reproduction studies have been performed on mice and rats using oral doses of cephalexin monohydrate 0.6 and 1.5 times the maximum daily human dose (66 mg/kg/day) based upon mg/m^2, and have revealed no harm to the fetus. There are, however, no adequate and well-controlled studies in pregnant women. Because animal reproduction studies are not always predictive of human response, this drug should be used during pregnancy only if clearly needed.

Nursing Mothers

The excretion of cephalexin in human milk increased up to 4 hours after a 500 mg dose; the drug reached a maximum level of 4 µg/mL, then decreased gradually, and had disappeared 8 hours after administration. Caution should be exercised when cephalexin capsule is administered to a nursing woman.

Pediatric Use

The safety and effectiveness of cephalexin in pediatric patients was established in clinical trials for the dosages described in the DOSAGE AND ADMINISTRATIONsection. In these trials, pediatric patients may have received cephalexin capsules or cephalexin for oral suspension. Cephalexin capsules should only be used in children and adolescents capable of ingesting the capsule.

Geriatric Use

Of the 701 subjects in 3 published clinical studies of cephalexin, 433 (62%) were 65 and over. No overall differences in safety or effectiveness were observed between these subjects and younger subjects, and other reported clinical experience has not identified differences in responses between the elderly and younger patients, but greater sensitivity of some older individuals cannot be ruled out.

This drug is known to be substantially excreted by the kidney, and the risk of toxic reactions to this drug may be greater in patients with impaired renal function. Because elderly patients are more likely to have decreased renal function, care should be taken in dose selection, and it may be useful to monitor renal function (see PRECAUTIONS, Generalsection).

ADVERSE REACTIONS

Gastrointestinal— Onset of pseudomembranous colitis may occur during or after antibacterial treatment (See WARNINGSsection). Nausea and vomiting have been reported rarely. The most frequent side effect has been diarrhea. It was very rarely severe enough to warrant cessation of therapy. Dyspepsia, gastritis, and abdominal pain have also occurred. As with some penicillins and some other cephalosporins, transient hepatitis and cholestatic jaundice have been reported rarely.

Hypersensitivity— Allergic reactions in the form of rash, urticaria, angioedema, and, rarely, erythema multiforme, Stevens-Johnson syndrome, or toxic epidermal necrolysis have been observed. These reactions usually subsided upon discontinuation of the drug. In some of these reactions, supportive therapy may be necessary. Anaphylaxis has also been reported.

Other reactions have included genital and anal pruritus, genital moniliasis, vaginitis and vaginal discharge, dizziness, fatigue, headache, agitation, confusion, hallucinations, arthralgia, arthritis, and joint disorder. Reversible interstitial nephritis has been reported rarely. Eosinophilia, neutropenia, thrombocytopenia, hemolytic anemia, and slight elevations in AST and ALT have been reported.

In addition to the adverse reactions listed above that have been observed in patients treated with cephalexin, the following adverse reactions and altered laboratory tests have been reported for cephalosporin class antibiotics:

- Adverse Reactions— Fever, colitis, aplastic anemia, hemorrhage, renal dysfunction, and toxic nephropathy.

- Several cephalosporins have been implicated in triggering seizures, particularly in patients with renal impairment when the dosage was not reduced (see INDICATIONS AND USAGEand PRECAUTIONS, Generalsection). If seizures associated with drug therapy should occur, the drug should be discontinued. Anticonvulsant therapy can be given if clinically indicated.

- Altered Laboratory Tests— Prolonged prothrombin time, increased BUN, increased creatinine, elevated alkaline phosphatase, elevated bilirubin, elevated LDH, pancytopenia, leukopenia, and agranulocytosis.

OVERDOSAGE

Signs and Symptoms— Symptoms of oral overdose may include nausea, vomiting, epigastric distress, diarrhea, and hematuria. If other symptoms are present, it is probably secondary to an underlying disease state, an allergic reaction, or toxicity due to ingestion of a second medication.

Treatment— To obtain up-to-date information about the treatment of overdose, a good resource is your certified Regional Poison Control Center. Telephone numbers of certified poison control centers are listed in the Physicians’ Desk Reference (PDR).In managing overdosage, consider the possibility of multiple drug overdoses, interaction among drugs, and unusual drug kinetics in your patient.

Unless 5 to 10 times the normal dose of cephalexin has been ingested, gastrointestinal decontamination should not be necessary.

Protect the patient’s airway and support ventilation and perfusion. Meticulously monitor and maintain, within acceptable limits, the patient’s vital signs, blood gases, serum electrolytes, etc. Absorption of drugs from the gastrointestinal tract may be decreased by giving activated charcoal, which, in many cases, is more effective than emesis or lavage; consider charcoal instead of or in addition to gastric emptying. Repeated doses of charcoal over time may hasten elimination of some drugs that have been absorbed. Safeguard the patient’s airway when employing gastric emptying or charcoal.

Forced diuresis, peritoneal dialysis, hemodialysis, or charcoal hemoperfusion have not been established as beneficial for an overdose of cephalexin; however, it would be extremely unlikely that one of these procedures would be indicated.

The oral median lethal dose of cephalexin in rats is >5000 mg/kg.

DOSAGE AND ADMINISTRATION

Cephalexin capsules are administered orally.

Adults— The adult dosage ranges from 1 to 4 g daily in divided doses. The 333 mg and the 750 mg strengths should be administered such that the daily dose is within 1 to 4 grams per day. The usual adult dose is 250 mg every 6 hours. For the following infections, a dosage of 500 mg may be administered every 12 hours: streptococcal pharyngitis, skin and skin structure infections, and uncomplicated cystitis in patients over 15 years of age. Cystitis therapy should be continued for 7 to 14 days. For more severe infections or those caused by less susceptible organisms, larger doses may be needed. If daily doses of cephalexin greater than 4 g are required, parenteral cephalosporins, in appropriate doses, should be considered.

Pediatric Patients— The usual recommended daily dosage for pediatric patients is 25 to 50 mg/kg in divided doses. For streptococcal pharyngitis in patients over 1 year of age and for skin and skin structure infections, the total daily dose may be divided and administered every 12 hours.

In severe infections, the dosage may be doubled.

In the therapy of otitis media, clinical studies have shown that a dosage of 75 to 100 mg/kg/day in 4 divided doses is required.

In the treatment of β-hemolytic streptococcal infections, a therapeutic dosage of cephalexin should be administered for at least 10 days.

HOW SUPPLIED

Cephalexin capsules, USP are available in:

The 250 mg capsules are a white to off white powder filled into size 2 capsules (white opaque cap and white opaque body) that are imprinted with 801 on the cap in black. They are available as follows:

Bottles of 100 NDC 62250-801-02

Bottles of 500 NDC 62250-801-08

The 500 mg capsules are a white to off white powder filled into size 0 capsules (white opaque cap and white opaque body) that are imprinted with 802 on the cap in black. They are available as follows:

Bottles of 100 NDC 62250-802-02

Bottles of 500 NDC 62250-802-08

Store at 20°C to 25°C (68°F to 77°F) [see USP Controlled Room Temperature].

REFERENCES

1. National Committee for Clinical Laboratory Standards. Methods for Dilution Antimicrobial Susceptibility Tests for Bacteria that Grow Aerobically — Fourth Edition. Approved Standard NCCLS Document M7-A4, Vol. 17, No. 2, NCCLS, Wayne, PA, January, 1997.
2. National Committee for Clinical Laboratory Standards. Performance Standards for Antimicrobial Disk Susceptibility Tests — Sixth Edition. Approved Standard NCCLS Document M2-A6, Vol. 17, No. 1, NCCLS, Wayne, PA, January, 1997.
3. National Committee for Clinical Laboratory Standards. Performance Standards for Antimicrobial Susceptibility Testing — Eighth Informational Supplement. Approved Standard NCCLS Document M100-S8, Vol. 18, No. 1, NCCLS, Wayne, PA, January, 1998.

Literature revised May 2011

Manufactured by:
Belcher Pharmaceuticals, LLC.
Largo, Florida 33773

May 2011 L02I R-0909A

PACKAGE LABEL.PRINCIPAL DISPLAY PANEL

Bottles of 100 NDC 62250-801-02

Bottles of 500 NDC 62250-801-08

Bottles of 100 NDC 62250-802-02

Bottles of 500 NDC 62250-802-08